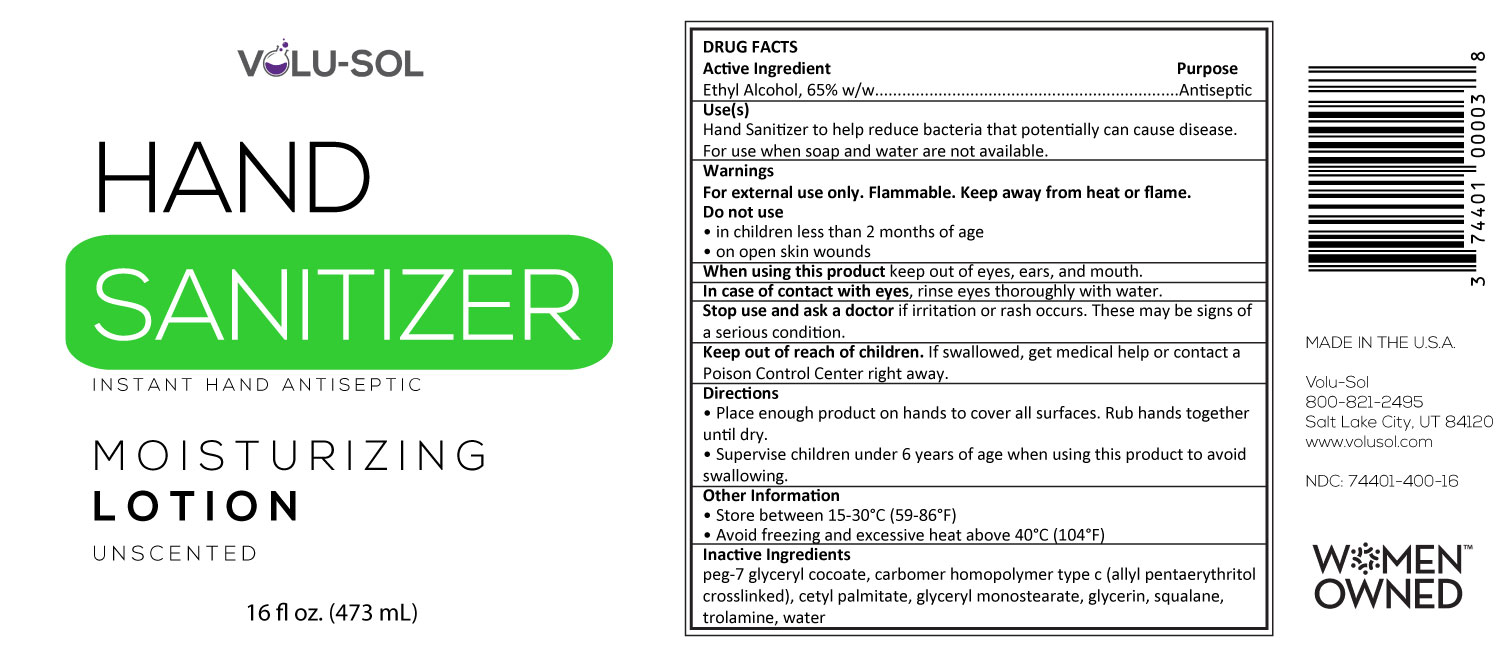 DRUG LABEL: Volu-Sol Moisturizing Hand Sanitizer
NDC: 74401-400 | Form: LOTION
Manufacturer: Volu-Sol
Category: otc | Type: HUMAN OTC DRUG LABEL
Date: 20250113

ACTIVE INGREDIENTS: ALCOHOL 540.7 mg/1 mL
INACTIVE INGREDIENTS: CARBOMER HOMOPOLYMER TYPE C (ALLYL PENTAERYTHRITOL CROSSLINKED) 5.5 mg/1 mL; PEG-7 GLYCERYL COCOATE 23.6 mg/1 mL; TROLAMINE 7.9 mg/1 mL; GLYCERIN 8.2 mg/1 mL; SQUALANE 5.7 mg/1 mL; WATER; CETYL PALMITATE 6 mg/1 mL; GLYCERYL MONOSTEARATE 15 mg/1 mL

Active Ingredient(s)

Ethyl Alcohol, 65% w/w. Purpose: Antiseptic

Purpose

Antiseptic, Hand Sanitizer

Use

Hand Sanitizer to help reduce bacteria that potentially can cause disease. For use when soap and water are not available.

Warnings

For external use only. Flammable. Keep away from heat or flame

Do not use

- in children less than 2 months of age
- on open skin wounds

When using this product keep out of eyes, ears, and mouth. In case of contact with eyes, rinse eyes thoroughly with water.
Stop use and ask a doctor if irritation or rash occurs. These may be signs of a serious condition.
Keep out of reach of children. If swallowed, get medical help or contact a Poison Control Center right away.

Stop use and ask a doctor if irritation or rash occurs. These may be signs of a serious condition.

Keep out of reach of children. If swallowed, get medical help or contact a Poison Control Center right away.

Directions

- Place enough product on hands to cover all surfaces. Rub hands together until dry.
- Supervise children under 6 years of age when using this product to avoid swallowing.

Other information

- Store between 15-30C (59-86F)
- Avoid freezing and excessive heat above 40C (104F)

Inactive ingredients

peg-7 glyceryl cocoate, carbomer homopolymer type c (allyl pentaerythritol crosslinked), cetyl palmitate, glyceryl monostearate, glycerin, squalane, trolamine, water

Package Label - Principal Display Panel

473 mL NDC: 74401-400-16